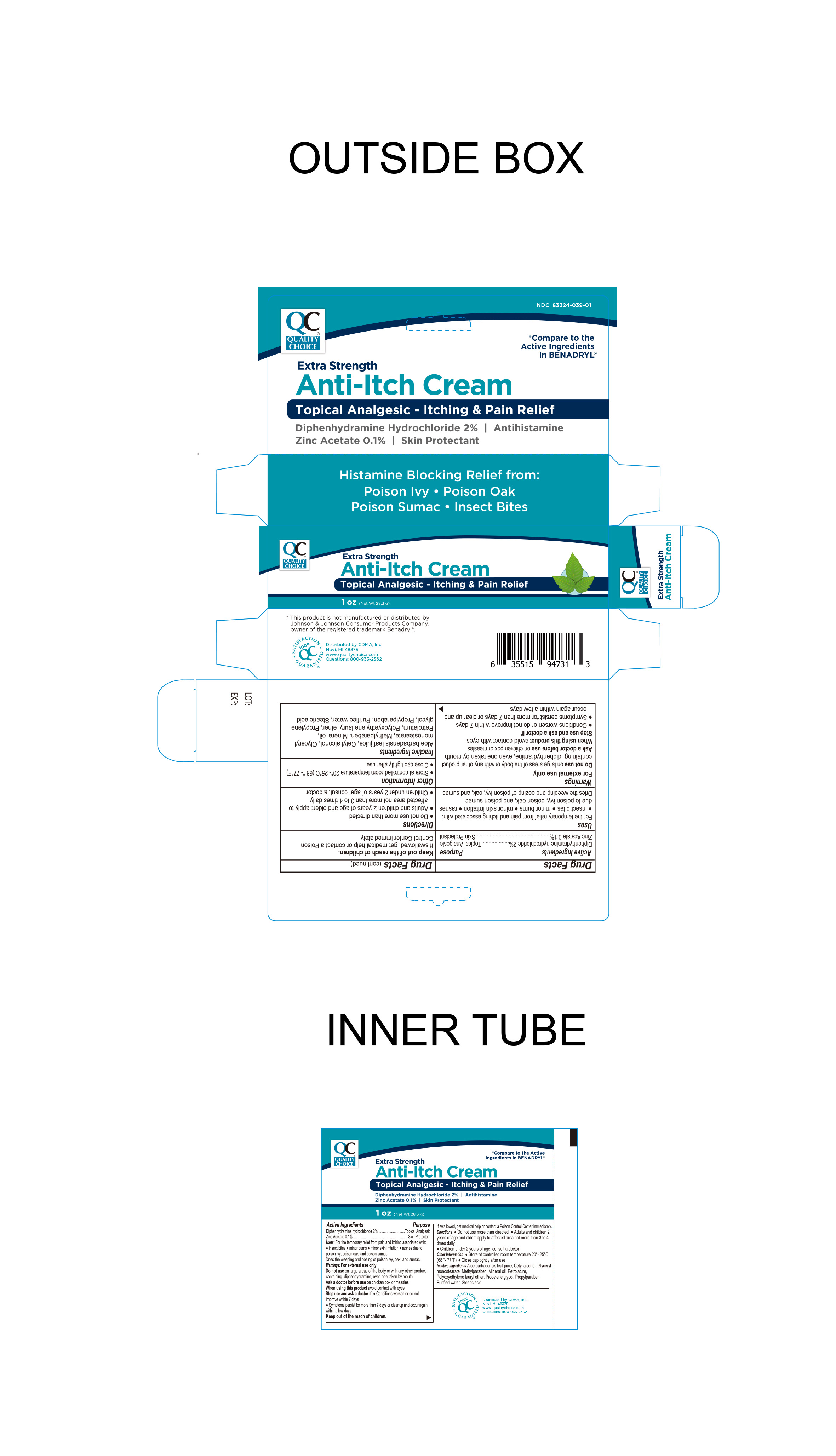 DRUG LABEL: Anti-Itch Cream
NDC: 83324-039 | Form: CREAM
Manufacturer: Chain Drug Marketing Association Inc.
Category: otc | Type: HUMAN OTC DRUG LABEL
Date: 20250109

ACTIVE INGREDIENTS: DIPHENHYDRAMINE HYDROCHLORIDE 2 g/100 g; ZINC ACETATE 0.1 g/100 g
INACTIVE INGREDIENTS: LAURETH-23; WATER; PETROLATUM; MINERAL OIL; METHYLPARABEN; PROPYLENE GLYCOL; STEARIC ACID; GLYCERYL MONOSTEARATE; PROPYLPARABEN; ALOE VERA LEAF; CETYL ALCOHOL

Quality Choice Extra Strength Anti-Itch Cream

Active Ingredient

Diphenhydramine Hydrochloride 2%

Purpose

Topical Analgesic

Active Ingredient

Zinc Acetate 0.1%

Purpose

Skin Protectant

INDICATIONS AND USAGE

For the temporary relief from pain and itching associated with

- insect bites
- minor burns
- minor skin irritation
- rashes due to poison ivy, poison oak, and poison sumac
- dries the weeping and oozing of poison ivy, oak and sumac

Warnings

For External Use Only

Do not useon large areas of the body or with any other product containing diphenhydramine, even one taken by mouth

Ask a doctor before use on chicken pox or measles

When using this productavoid contact with eyes

Stop use and ask a doctor if

- Conditions worsen or do not improve within 7 days
- Symptoms persist for more than 7 days or clear up and occur again within a few days

Stop use and ask a doctor

- Conditions worsen or do not improve within 7 days
- Symptoms persist for more than 7 days or clear up and occur again within a few days

Keep out of the reach of children

If swallowed, get medical help or contact a Poison Control Center immediately

Directions

- Do not use more than directed
- Adults and children 2 years of age and older: apply to affected area not more than 3 to 4 times daily
- Children under 2 years of age: consult a doctor

Other information

- Store at controlled room temperature 20º-25ºC (68º-77ºF)
- Close cap tightly after use

Questions?Call 1-800-935-2362

Inactive Ingredients

Aloe Vera (Aloe Barbadensis) leaf juice, Cetyl alcohol, Glyceryl monostearate, Methylparaben, Mineral Oil, Petrolatum, Polyoxyethylene lauryl ether, Propylene glycol, Propylparaben, Purified Water, Stearic acid

Distributed By

Distributed by CDMA Inc.

Novi, MI 48375

www.qualitychoice.com

Questions: 800-935-2362

This product is not manufactured or distributed by Johnson & Johnson Consumer Products Company owner of the registered trademark Benadryl.